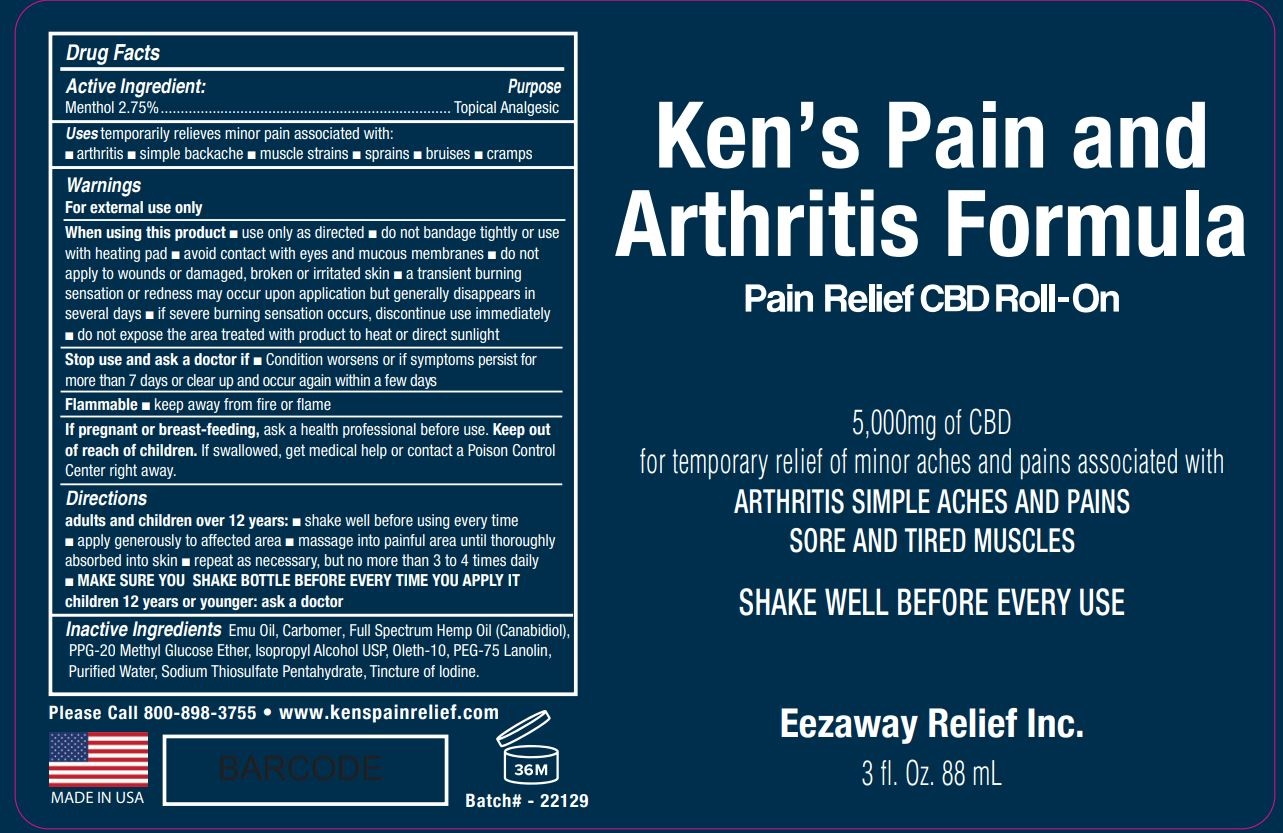 DRUG LABEL: KENS PAIN AND ARTHRITIS FORMULA
NDC: 69678-143 | Form: LIQUID
Manufacturer: Eezaway Relief Inc
Category: otc | Type: HUMAN OTC DRUG LABEL
Date: 20250717

ACTIVE INGREDIENTS: MENTHOL, UNSPECIFIED FORM 2.75 g/100 mL
INACTIVE INGREDIENTS: EMU OIL; CARBOMER HOMOPOLYMER, UNSPECIFIED TYPE; CANNABIS SATIVA SEED OIL; PPG-20 METHYL GLUCOSE ETHER; ISOPROPYL ALCOHOL; OLETH-10; PEG-75 LANOLIN; WATER; SODIUM THIOSULFATE; IODINE

Kens Pain and Arthritis Formula

Active Ingredient:

Menthol 2.75%

Purpose

Topical Analgesic

Uses

temporarily relieves minor pain associated with:

• arthritis • simple backache • muscle strains • sprains • bruises • cramps

Warnings

For external use only

When using this product • use only as directed • do not bandage tightly or use with heating pad • avoid contact with eyes and mucous membranes • do not apply to wounds or damaged, broken or irritated skin • a transient burning sensation or redness may occur upon application but generally disappears in several days • if severe burning sensation occurs, discontinue use immediately • do not expose the area treated with product to heat or direct sunlight

Stop use and ask a doctor if • Condition worsens or if symptoms persist for more than 7 days or clear up and occur again within a few days

Flammable • keep away from fire or flame

If pregnant or breast-feeding, ask a health professional before use.

Keep out of reach of children. If swallowed, get medical help or contact a Poison Control Center right away.

Directions

adults and children over 12 years: • shake well before using every time • apply generously to affected area • massage into painful area until thoroughly absorbed into skin • repeat as necessary, but no more than 3 to 4 times daily

• MAKE SURE YOU SHAKE BOTTLE BEFORE EVERY TIME YOU APPLY IT

children 12 years or younger: ask a doctor

Inactive Ingredients

Emu Oil, Carbomer, Full Spectrum Hemp Oil (Cannabidiol), PPG-20 Methyl Glucose Ether, Isopropyl Alcohol USP, Oleth-10, PEG-75 Lanolin, Purified Water, Sodium Thiosulfate Pentahydrate, Tincture of Iodine.

Pain Relief CBD Roll-On

5,000mg of CBD

for temporary relief of minor aches and pains associated with

ARTHRITIS SIMPLE ACHES AND PAINS
SORE AND TIRED MUSCLES

SHAKE WELL BEFORE EVERY USE

Eezaway Relief Inc.

Please Call 800-898-3755 www.kenspainrelief.com

MADE IN USA